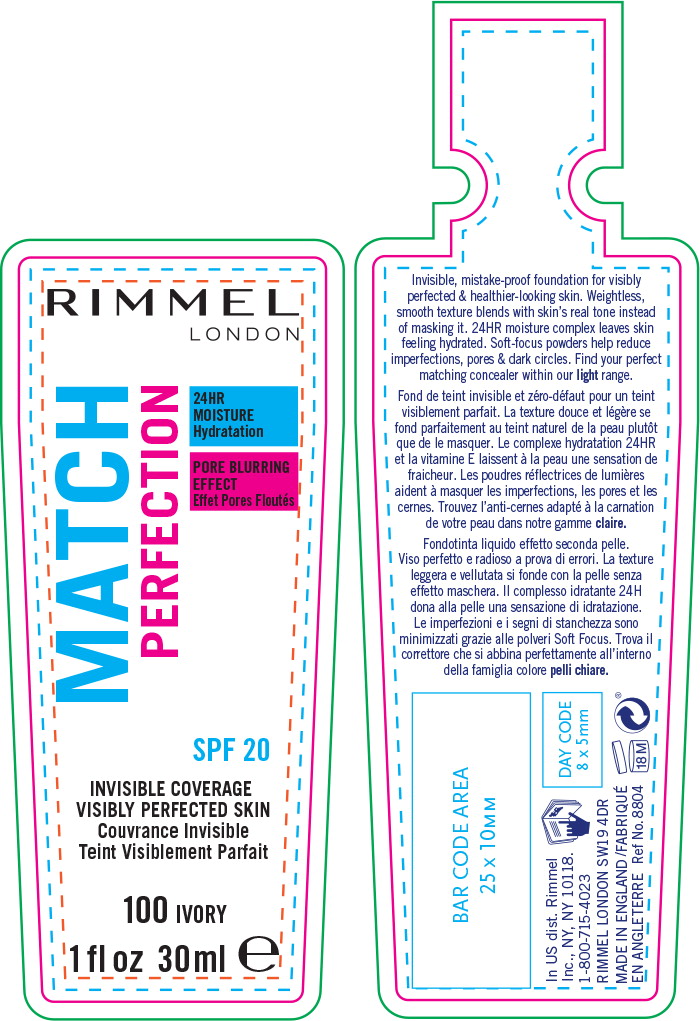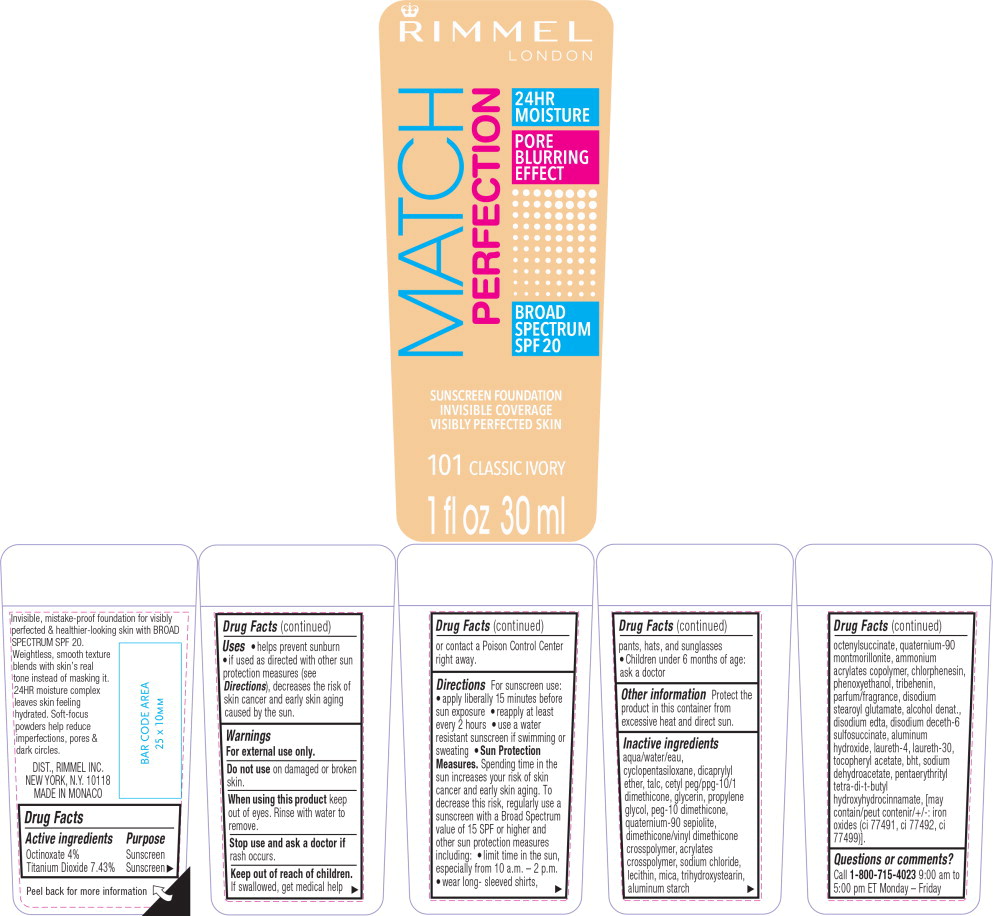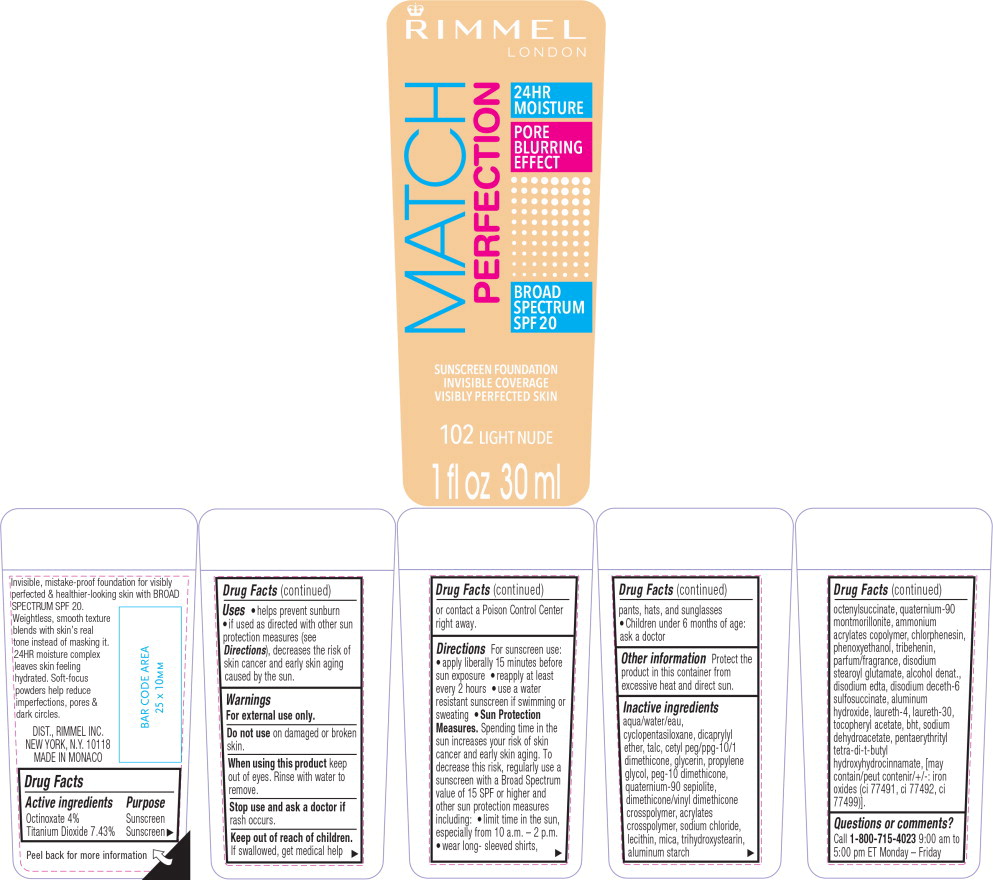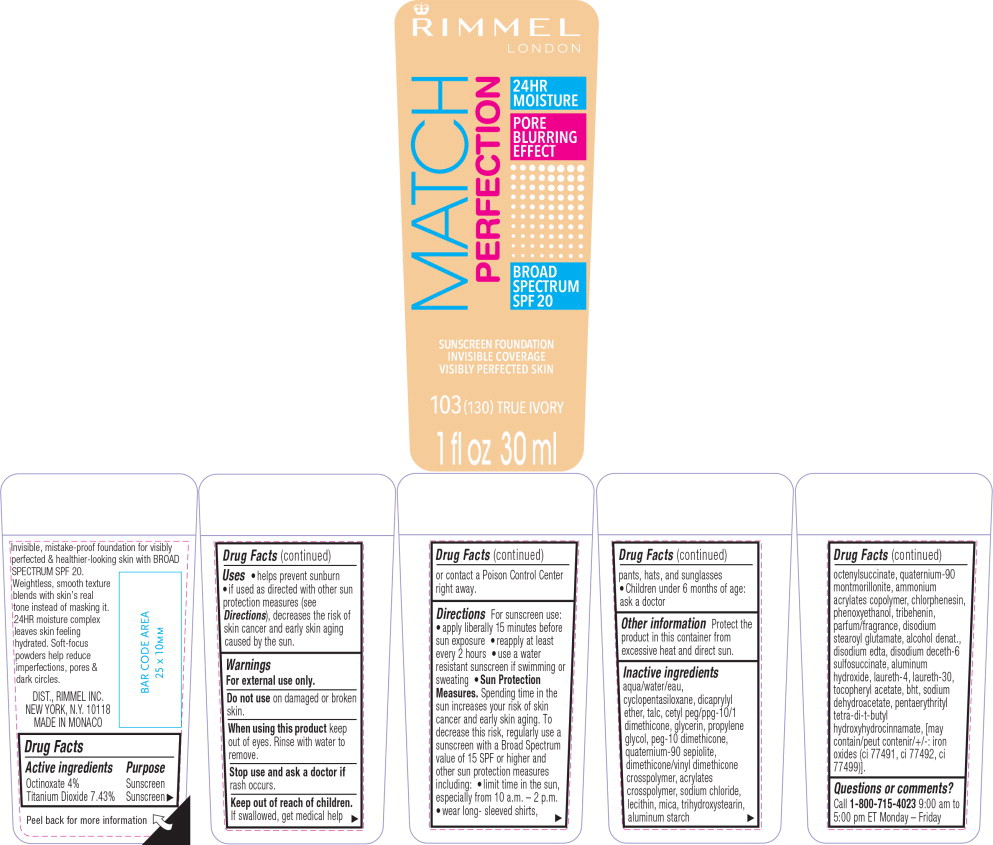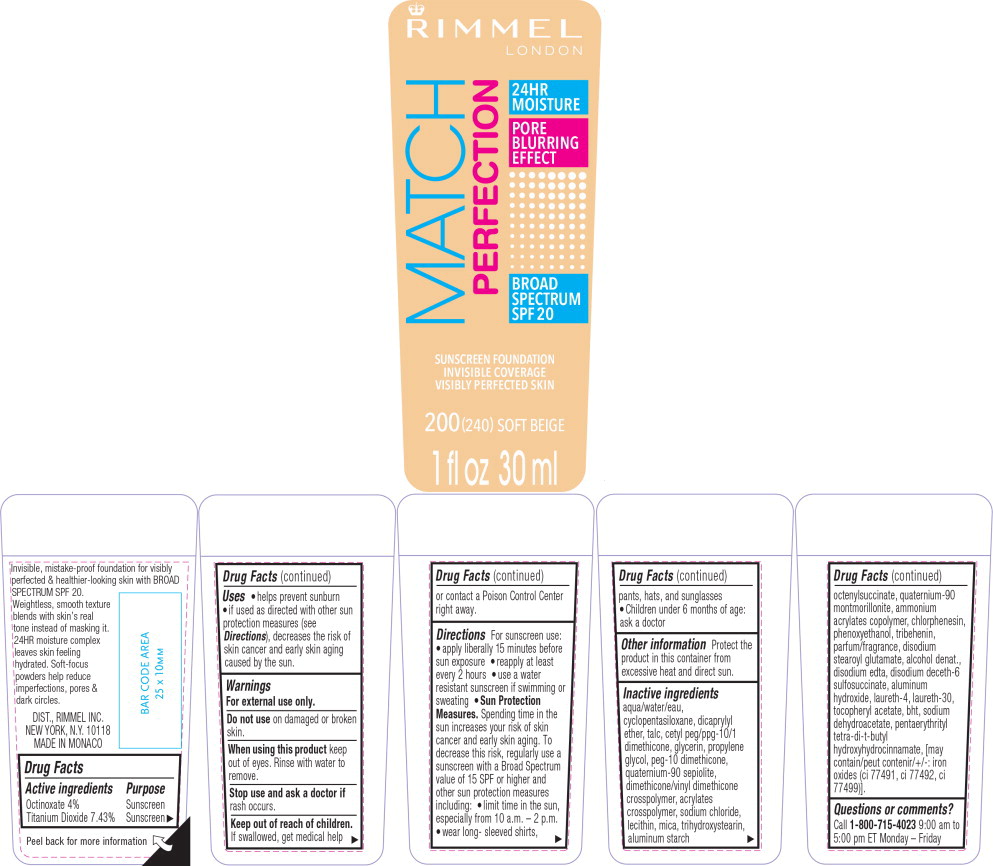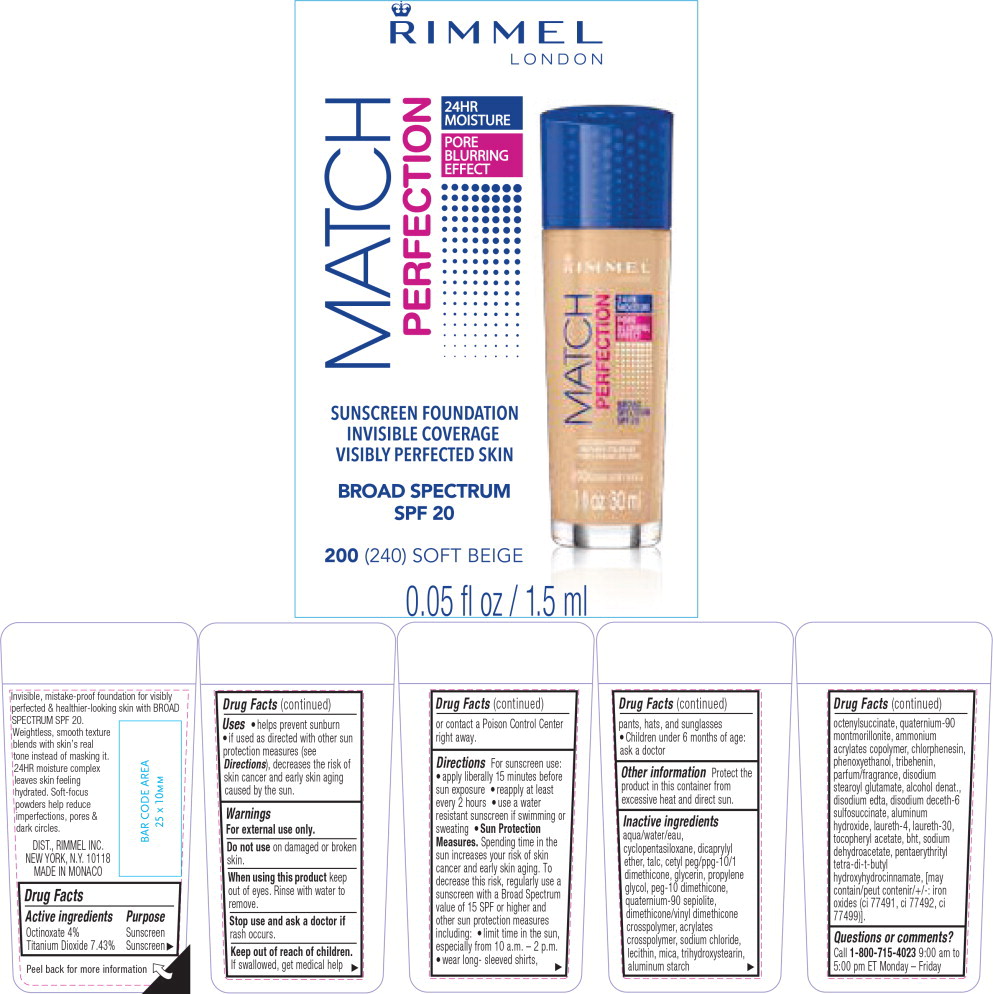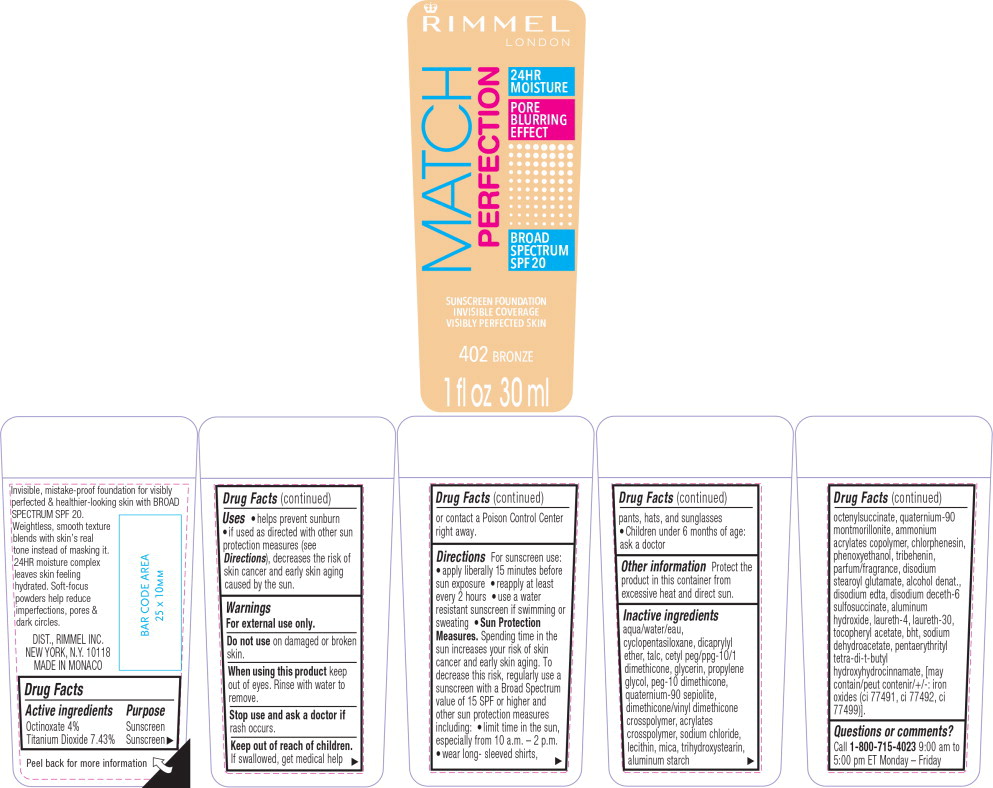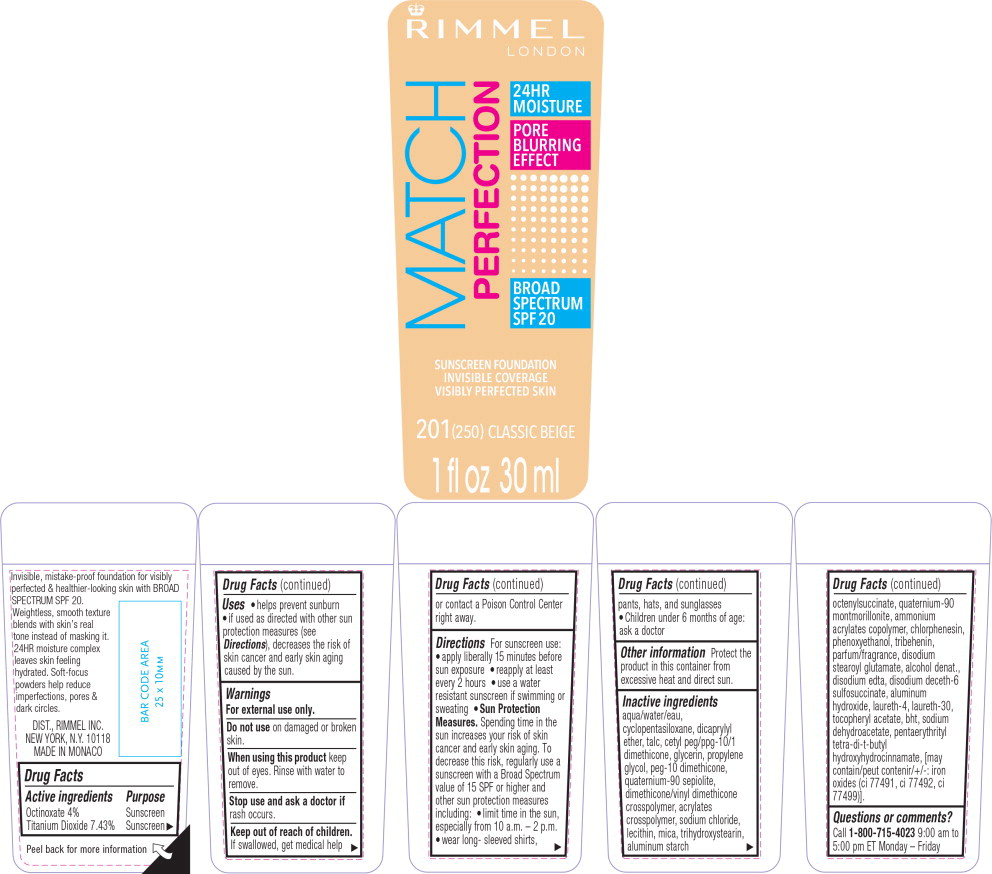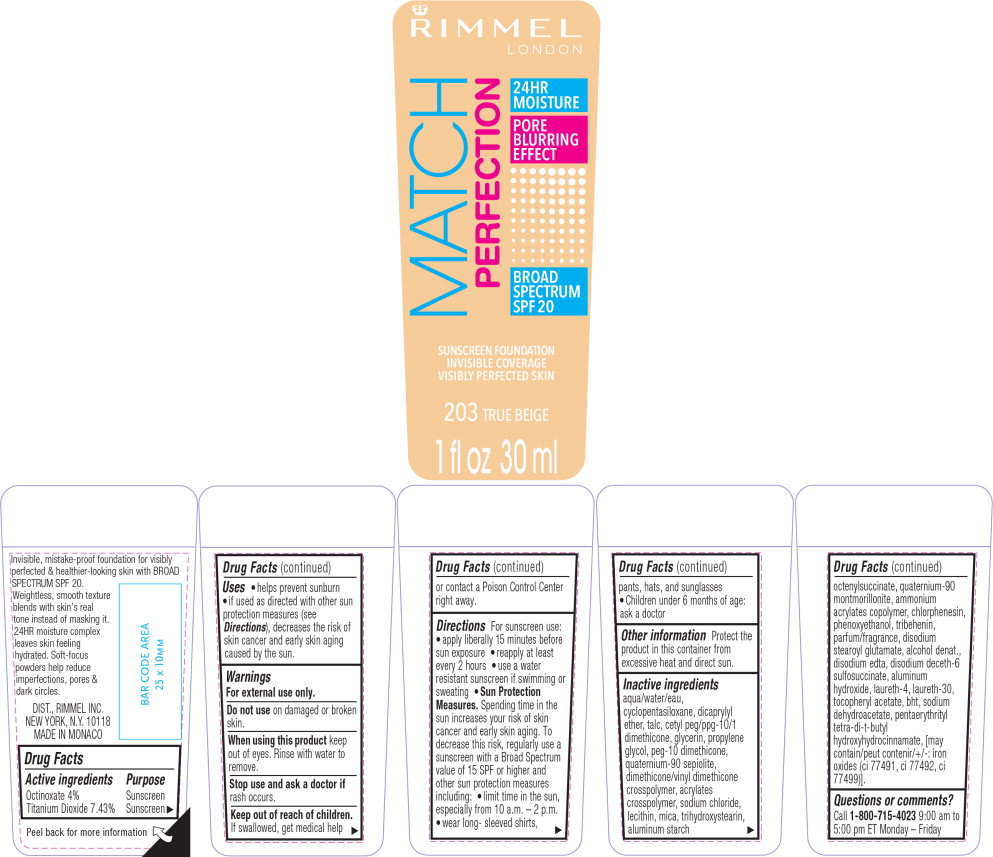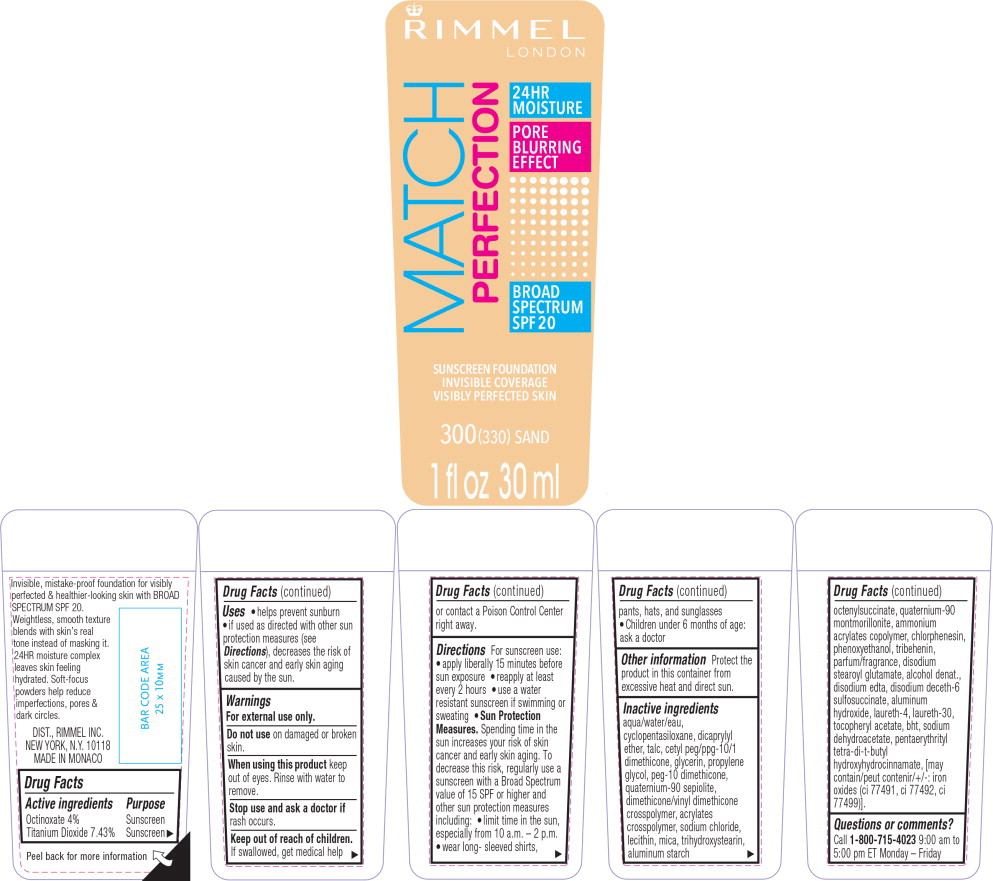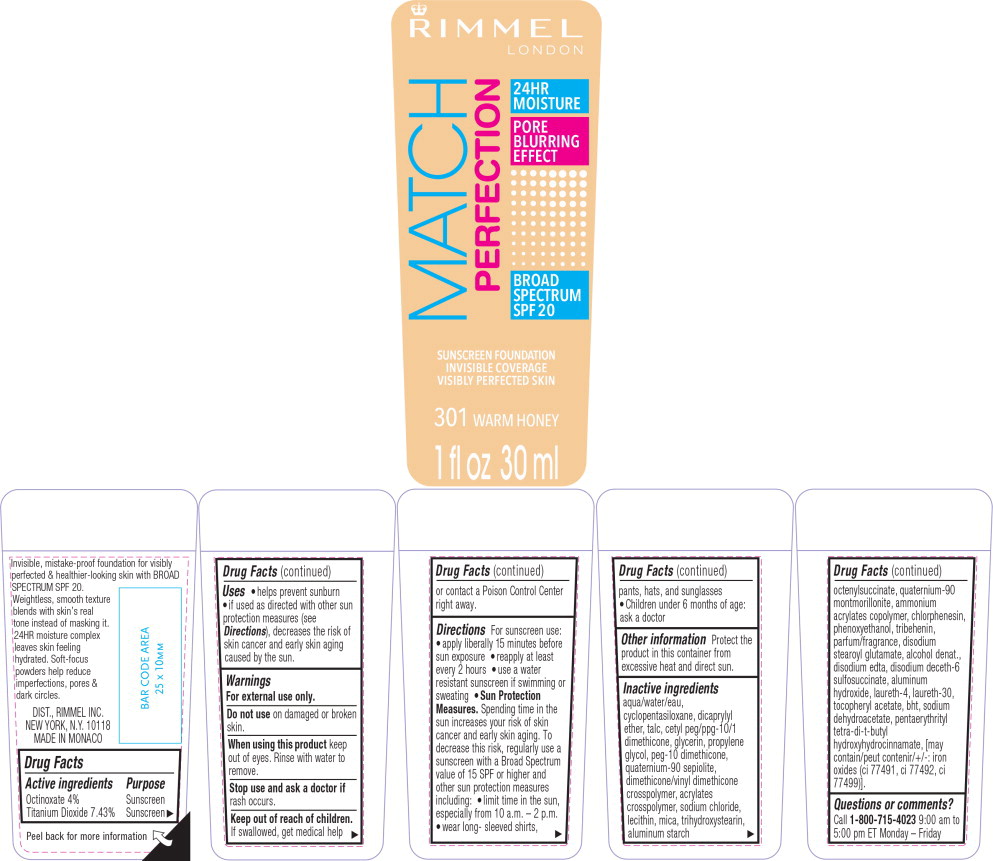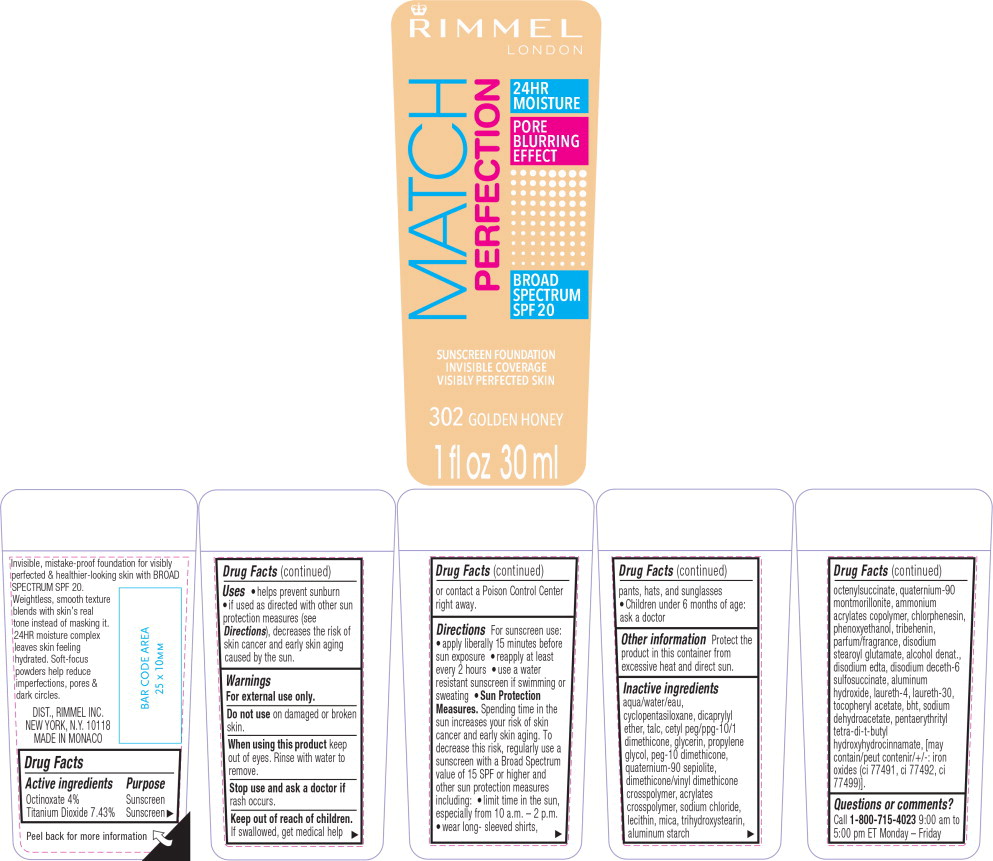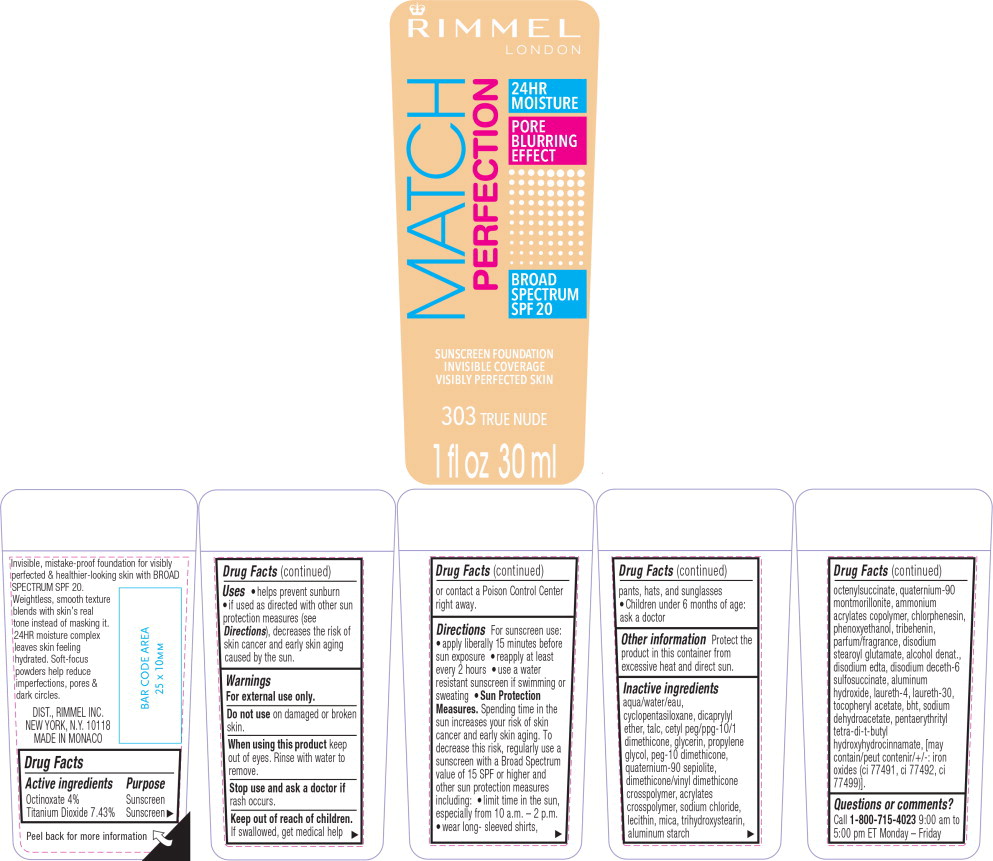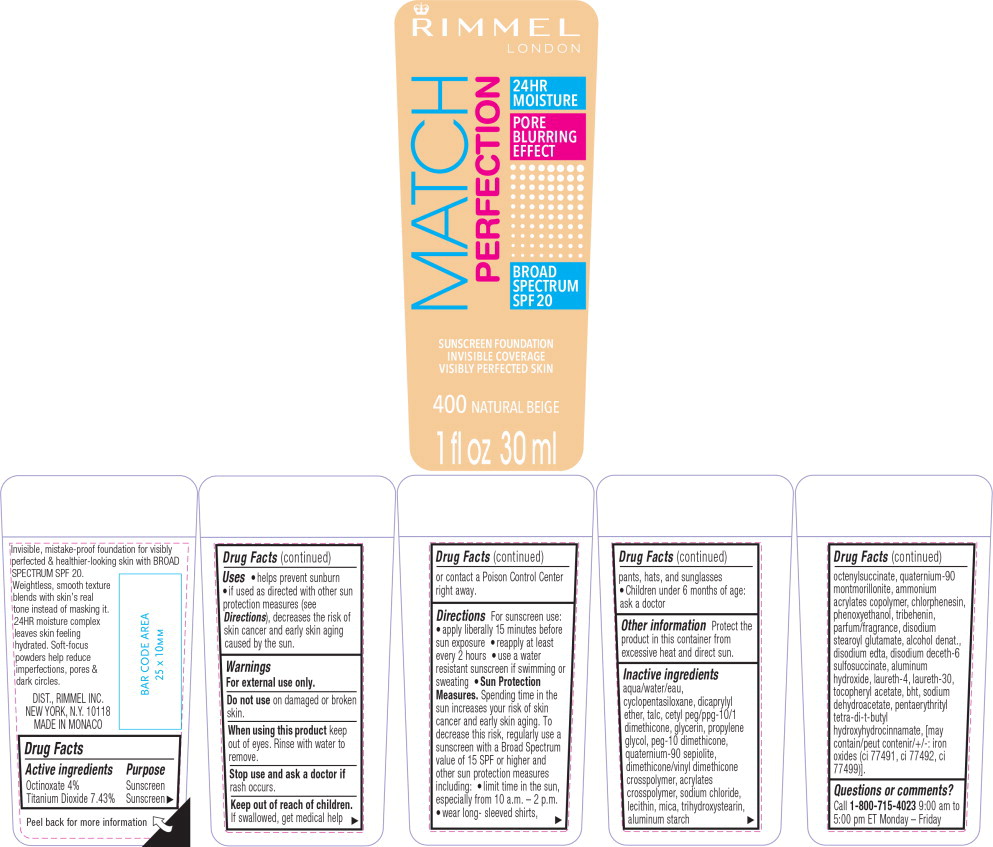 DRUG LABEL: MATCH PERFECTION Foundation SPF 20 - Shade 100
NDC: 76485-1050 | Form: LIQUID
Manufacturer: Rimmel Inc.
Category: otc | Type: HUMAN OTC DRUG LABEL
Date: 20201026

ACTIVE INGREDIENTS: OCTINOXATE 1.278 g/30 mL; TITANIUM DIOXIDE 2.374 g/30 mL
INACTIVE INGREDIENTS: WATER; CYCLOMETHICONE 5; TALC; DICAPRYLYL ETHER; CETYL PEG/PPG-10/1 DIMETHICONE (HLB 3); GLYCERIN; PROPYLENE GLYCOL; PEG-10 DIMETHICONE (600 CST); QUATERNIUM-91; DIMETHICONE/VINYL DIMETHICONE CROSSPOLYMER (HARD PARTICLE); SODIUM CHLORIDE; EGG PHOSPHOLIPIDS; MICA; TRIHYDROXYSTEARIN; ALUMINUM STARCH OCTENYLSUCCINATE; MONTMORILLONITE; AMMONIA; CHLORPHENESIN; PHENOXYETHANOL; TRIBEHENIN; DISODIUM STEAROYL GLUTAMATE; ALCOHOL; EDETATE DISODIUM; DECETH-6; ALUMINUM HYDROXIDE; LAURETH-4; LAURETH-30; .ALPHA.-TOCOPHEROL ACETATE; BUTYLATED HYDROXYTOLUENE; SODIUM DEHYDROACETATE; PENTAERYTHRITOL TETRAKIS(3-(3,5-DI-TERT-BUTYL-4-HYDROXYPHENYL)PROPIONATE); FERRIC OXIDE RED; FERRIC OXIDE YELLOW; FERROSOFERRIC OXIDE

Rimmel MATCH PERFECTION Foundation SPF 20

Drug Facts

Active ingredients

Octinoxate 4%

Titanium Dioxide 7.43%

Purpose

Sunscreen

Sunscreen

Uses

- helps prevent sunburn
- if used as directed with other sun protection measures (see Directions), decreases the risk of skin cancer and early skin aging caused by the sun.

Warnings

For external use only.

Do not use on damaged or broken skin.

When using this product keep out of eyes. Rinse with water to remove.

Stop use and ask a doctor if rash occurs.

Keep out of reach of children. If swallowed, get medical help or contact a Poison Control Center right away.

Directions

For sunscreen use:

- apply liberally 15 minutes before sun exposure
- reapply at least every 2 hours
- use a water resistant sunscreen if swimming or sweating
- Sun Protection Measures. Spending time in the sun increases your risk of skin cancer and early skin aging. To decrease this risk, regularly use a sunscreen with a Broad Spectrum value of 15 SPF or higher and other sun protection measures including: •limit time in the sun, especially from 10 a.m.-2 p.m.
- wear long- sleeved shirts, pants, hats, and sunglasses • Children under 6 months of age: ask a doctor

Other information

Protect the product in this container from excessive heat and direct sun.

Inactive ingredients

aqua/water/eau, cyclopentasiloxane, dicaprylyl ether, talc, cetyl peg/ppg-10/1 dimethicone, glycerin, propylene glycol, peg-10 dimethicone, quaternium-90 sepiolite, dimethicone/vinyl dimethicone crosspolymer, acrylates crosspolymer, sodium chloride, lecithin, mica, trihydroxystearin, aluminum starch octenylsuccinate, quaternium-90 montmorillonite, ammonium acrylates copolymer, chlorphenesin, phenoxyethanol, tribehenin, parfum/fragrance, disodium stearoyl glutamate, alcohol denat., disodium edta, disodium deceth-6 sulfosuccinate, aluminum hydroxide, laureth-4, hexyl cinnamal, laureth-30, limonene, tocopheryl acetate, butylphenyl methylpropional, benzyl salicylate, linalool, geraniol, bht, sodium dehydroacetate, citronellol, alpha-isomethyl ionone, pentaerythrityl tetra-di-t-butyl hydroxyhydrocinnamate, [may contain/peut contenir/+/-: iron oxides (ci 77491, ci 77492, ci 77499)].

Questions or comments?

Call 1- 800- 715-4023 9:00 am to 5:00 pm ET Monday - Friday

Principal Display Panel - Bottle Label

RIMMEL

LONDON

MATCH
PERFECTION

24HR
MOISTURE

PORE
BLURRING
EFFECT

BROAD
SPECTRUM
SPF 20

SUNSCREEN FOUNDATION

INVISIBLE COVERAGE

VISIBLY PERFECTED SKIN

100 (120) IVORY

1 fl oz 30 ml

Principal Display Panel - Bottle Label

RIMMEL

LONDON

MATCH
PERFECTION

24HR
MOISTURE

PORE
BLURRING
EFFECT

BROAD
SPECTRUM
SPF 20

SUNSCREEN FOUNDATION

INVISIBLE COVERAGE

VISIBLY PERFECTED SKIN

101 CLASSIC IVORY

1 fl oz 30 ml

Principal Display Panel - Bottle Label

RIMMEL

LONDON

MATCH
PERFECTION

24HR
MOISTURE

PORE
BLURRING
EFFECT

BROAD
SPECTRUM
SPF 20

SUNSCREEN FOUNDATION

INVISIBLE COVERAGE

VISIBLY PERFECTED SKIN

102 LIGHT NUDE

1 fl oz 30 ml

Principal Display Panel - Bottle Label

RIMMEL

LONDON

MATCH
PERFECTION

24HR
MOISTURE

PORE
BLURRING
EFFECT

BROAD
SPECTRUM
SPF 20

SUNSCREEN FOUNDATION

INVISIBLE COVERAGE

VISIBLY PERFECTED SKIN

103 (130) TRUE IVORY

1 fl oz 30 ml

Principal Display Panel - Bottle Label

RIMMEL

LONDON

MATCH
PERFECTION

24HR
MOISTURE

PORE
BLURRING
EFFECT

BROAD
SPECTRUM
SPF 20

SUNSCREEN FOUNDATION

INVISIBLE COVERAGE

VISIBLY PERFECTED SKIN

200 (240) SOFT BEIGE

1 fl oz 30 ml

Principal Display Panel - Bottle Label

RIMMEL

LONDON

MATCH
PERFECTION

24 HR
MOISTURE

PORE
BLURRING
EFFECT

SUNSCREEN FOUNDATION

INVISIBLE COVERAGE

VISIBLY PERFECTED SKIN

BROAD SPECTRUM
SPF 20

200 (240) SOFT BEIGE

0.05 fl oz / 1.5 ml

Principal Display Panel - Bottle Label

RIMMEL

LONDON

MATCH
PERFECTION

24HR
MOISTURE

PORE
BLURRING
EFFECT

BROAD
SPECTRUM
SPF 20

SUNSCREEN FOUNDATION

INVISIBLE COVERAGE

VISIBLY PERFECTED SKIN

402 BRONZE

1 fl oz 30 ml

Principal Display Panel - Bottle Label

RIMMEL

LONDON

MATCH
PERFECTION

24HR
MOISTURE

PORE
BLURRING
EFFECT

BROAD
SPECTRUM
SPF 20

SUNSCREEN FOUNDATION

INVISIBLE COVERAGE

VISIBLY PERFECTED SKIN

201(250) CLASSIC BEIGE

1 fl oz 30 ml

Principal Display Panel - Bottle Label

RIMMEL

LONDON

MATCH
PERFECTION

24HR
MOISTURE

PORE
BLURRING
EFFECT

BROAD
SPECTRUM
SPF 20

SUNSCREEN FOUNDATION

INVISIBLE COVERAGE

VISIBLY PERFECTED SKIN

203 TRUE BEIGE

1 fl oz 30 ml

Principal Display Panel - Bottle Label

RIMMEL

LONDON

MATCH
PERFECTION

24HR
MOISTURE

PORE
BLURRING
EFFECT

BROAD
SPECTRUM
SPF 20

SUNSCREEN FOUNDATION

INVISIBLE COVERAGE

VISIBLY PERFECTED SKIN

300(330) SAND

1 fl oz 30 ml

Principal Display Panel - Bottle Label

RIMMEL

LONDON

MATCH
PERFECTION

24HR
MOISTURE

PORE
BLURRING
EFFECT

BROAD
SPECTRUM
SPF 20

SUNSCREEN FOUNDATION

INVISIBLE COVERAGE

VISIBLY PERFECTED SKIN

301 WARM HONEY

1 fl oz 30 ml

Principal Display Panel - Bottle Label

RIMMEL

LONDON

MATCH
PERFECTION

24HR
MOISTURE

PORE
BLURRING
EFFECT

BROAD
SPECTRUM
SPF 20

SUNSCREEN FOUNDATION

INVISIBLE COVERAGE

VISIBLY PERFECTED SKIN

302 GOLDEN HONEY

1 fl oz 30 ml

Principal Display Panel - Bottle Label

RIMMEL

LONDON

MATCH
PERFECTION

24HR
MOISTURE

PORE
BLURRING
EFFECT

BROAD
SPECTRUM
SPF 20

SUNSCREEN FOUNDATION

INVISIBLE COVERAGE

VISIBLY PERFECTED SKIN

303 TRUE NUDE

1 fl oz 30 ml

Principal Display Panel - Bottle Label

RIMMEL

LONDON

MATCH
PERFECTION

24HR
MOISTURE

PORE
BLURRING
EFFECT

BROAD
SPECTRUM
SPF 20

SUNSCREEN FOUNDATION

INVISIBLE COVERAGE

VISIBLY PERFECTED SKIN

400 NATURAL BEIGE

1 fl oz 30 ml